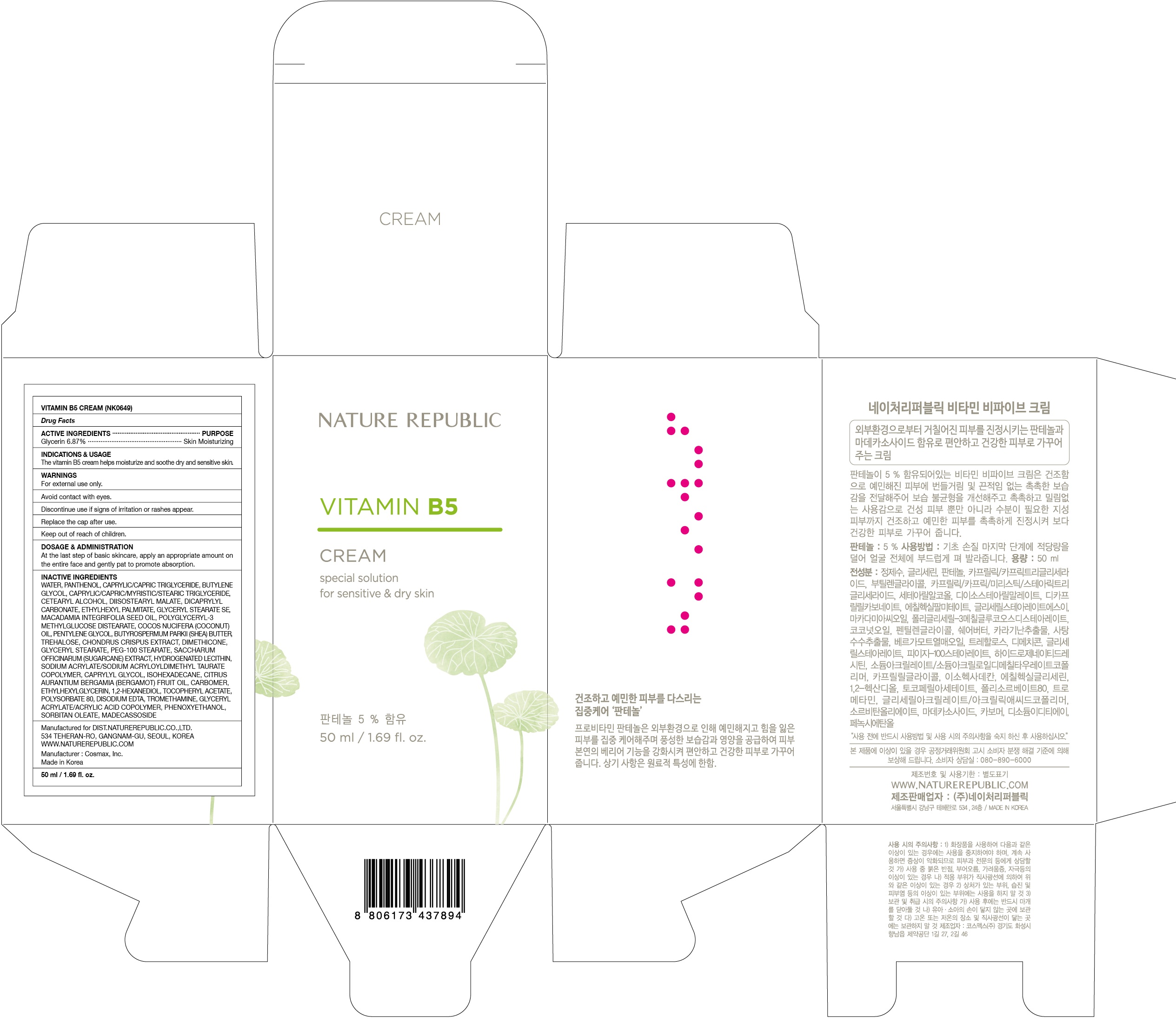 DRUG LABEL: VITAMIN B5
NDC: 51346-437 | Form: CREAM
Manufacturer: NATURE REPUBLIC CO., LTD.
Category: otc | Type: HUMAN OTC DRUG LABEL
Date: 20170120

ACTIVE INGREDIENTS: Glycerin 3.43 g/50 mL
INACTIVE INGREDIENTS: Water; Panthenol

ACTIVE INGREDIENT

Active ingredients: Glycerin 6.87%

INACTIVE INGREDIENT

Inactive ingredients: Water, Panthenol, Caprylic/Capric Triglyceride, Butylene Glycol, Caprylic/Capric/Myristic/Stearic Triglyceride, Cetearyl Alcohol, Diisostearyl Malate, Dicaprylyl Carbonate, Ethylhexyl Palmitate, Glyceryl Stearate SE, Macadamia Integrifolia Seed Oil, Polyglyceryl-3 Methylglucose Distearate, Cocos Nucifera (Coconut) Oil, Pentylene Glycol, Butyrospermum Parkii (Shea) Butter, Trehalose, Chondrus Crispus Extract, Dimethicone, Glyceryl Stearate, PEG-100 Stearate, Saccharum Officinarum (Sugarcane) Extract, Hydrogenated Lecithin, Sodium Acrylate/Sodium Acryloyldimethyl Taurate Copolymer, Caprylyl Glycol, Isohexadecane, Citrus Aurantium Bergamia (Bergamot) Fruit Oil, Carbomer, Ethylhexylglycerin, 1,2-Hexanediol, Tocopheryl Acetate, Polysorbate 80, Disodium EDTA, Tromethamine, Glyceryl Acrylate/Acrylic Acid Copolymer, Phenoxyethanol, Sorbitan Oleate, Madecassoside

PURPOSE

Purpose: Skin Moisturizing

WARNINGS

Warnings: For external use only. Avoid contact with eyes and mouth. Discontinue use if signs of irritation or rashes appear. Keep out of reach of children. Replace the cap after use.

KEEP OUT OF REACH OF CHILDREN

INDICATIONS & USAGE

Indications & Usage: The vitamin B5 cream helps moisturize and soothe dry and sensitive skin.

DOSAGE & ADMINISTRATION

Dosage & Administration: At the last step of basic skincare, apply an appropriate amount on the entire face and gently pat to promote absorption.